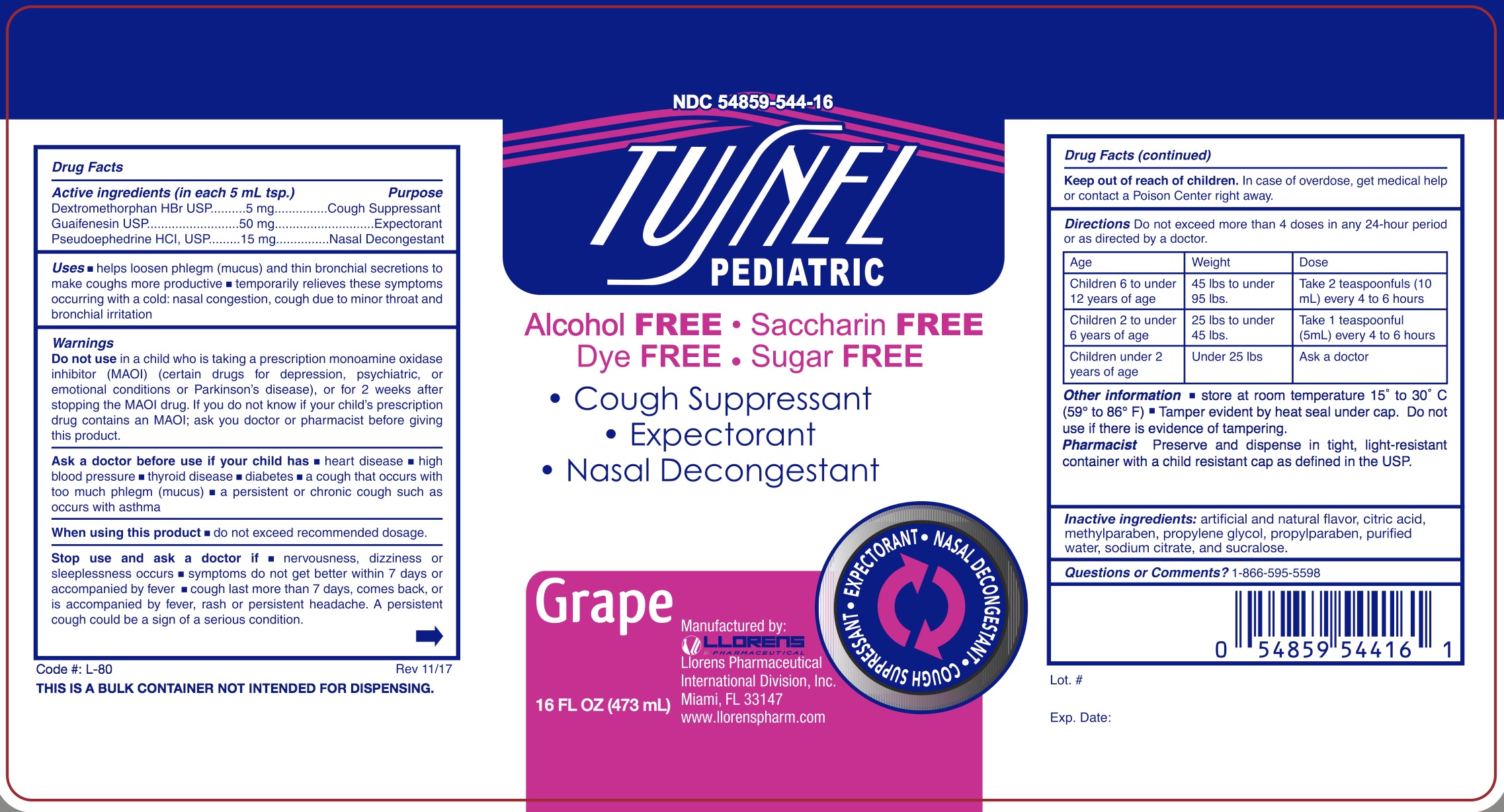 DRUG LABEL: Tusnel
NDC: 54859-544 | Form: LIQUID
Manufacturer: Llorens Pharmaceutical International Division
Category: otc | Type: HUMAN OTC DRUG LABEL
Date: 20251231

ACTIVE INGREDIENTS: DEXTROMETHORPHAN HYDROBROMIDE 5 mg/5 mL; GUAIFENESIN 50 mg/5 mL; PSEUDOEPHEDRINE HYDROCHLORIDE 15 mg/5 mL
INACTIVE INGREDIENTS: CITRIC ACID MONOHYDRATE; METHYLPARABEN; PROPYLENE GLYCOL; PROPYLPARABEN; WATER; SODIUM CITRATE; SUCRALOSE

Llorens-Tusnel Ped 544

Active Ingredients(in each 5 ml tsp.) Purpose

Dextromethorphan HBr........5mg..................................................Cough Suppressant

Guaifenesin........................50mg................................................Expectorant

Pseudoephedrine HCl..........15mg..................................................Nasal Decongestant

Purpose

Cough Suppressant

Expectorant

Nasal Decongestant

Warnings
Do not useif you are now taking a prescription monoamine oxidase inhibitor (MAOI) (certain drugs for depression, psychiatric, or emotional conditions, or Parkinson’s disease), or for 2 weeks after stopping the MAOI drug. If you do not know if your prescription drug contains an MAOI, ask a doctor or pharmacist before taking this product.

Ask a doctor before use if your child has

- heart disease
- high blood pressure
- thyroid disease
- diabetes
- a cough that occurs with too much phlegm (mucus)
- a persistent or chronic cough such as occurs with asthma

When using this product

- do not exceed recommended dosage

Stop use and ask a doctor if

- nervousness, dizziness or sleeplessness occurs
- symptoms do not get better within 7 days or accompanied by fever
- cough last more than 7 days, comes back, or is accompanied by fever, rash or persistent headache. A persistent cough could be a sign of a serious condition.

Keep out of reach of children.In case of overdose, get medical help or contact a Poison Control Center right away.

DOSAGE AND ADMINISTRATION

DirectionsDo not exceed more than 4 doses in any 24-hour period
or as directed by a doctor.

Age | Weight | Dose
Children 6 to under 12 years of age | 45 lbs to under 95 lbs | Take 2 teaspoonfuls (10 mL) every 4 to 6 hours
Children 2 to under 6 years of age | 25 lbs to under 45 lbs | Take 1 teaspoonful (5mL) every 4 to 6 hours
Children under 2 years of age | Under 25 lbs | ask a doctor

Uses

- helps loosen phlegm (mucus) and thin bronchial secretions to make coughs more productive
- temporarily relieves these symptoms occurring with a cold: nasal congestions, cough due to minor throat and bronchial irritation.

INACTIVE INGREDIENT

Inactive ingredients astificial and natural flavor, citric acid, methylparaben, propylene glycol, propylparaben, purified water, sodium citrate, and sucralos

Questions or Comments?1-866-595-5598